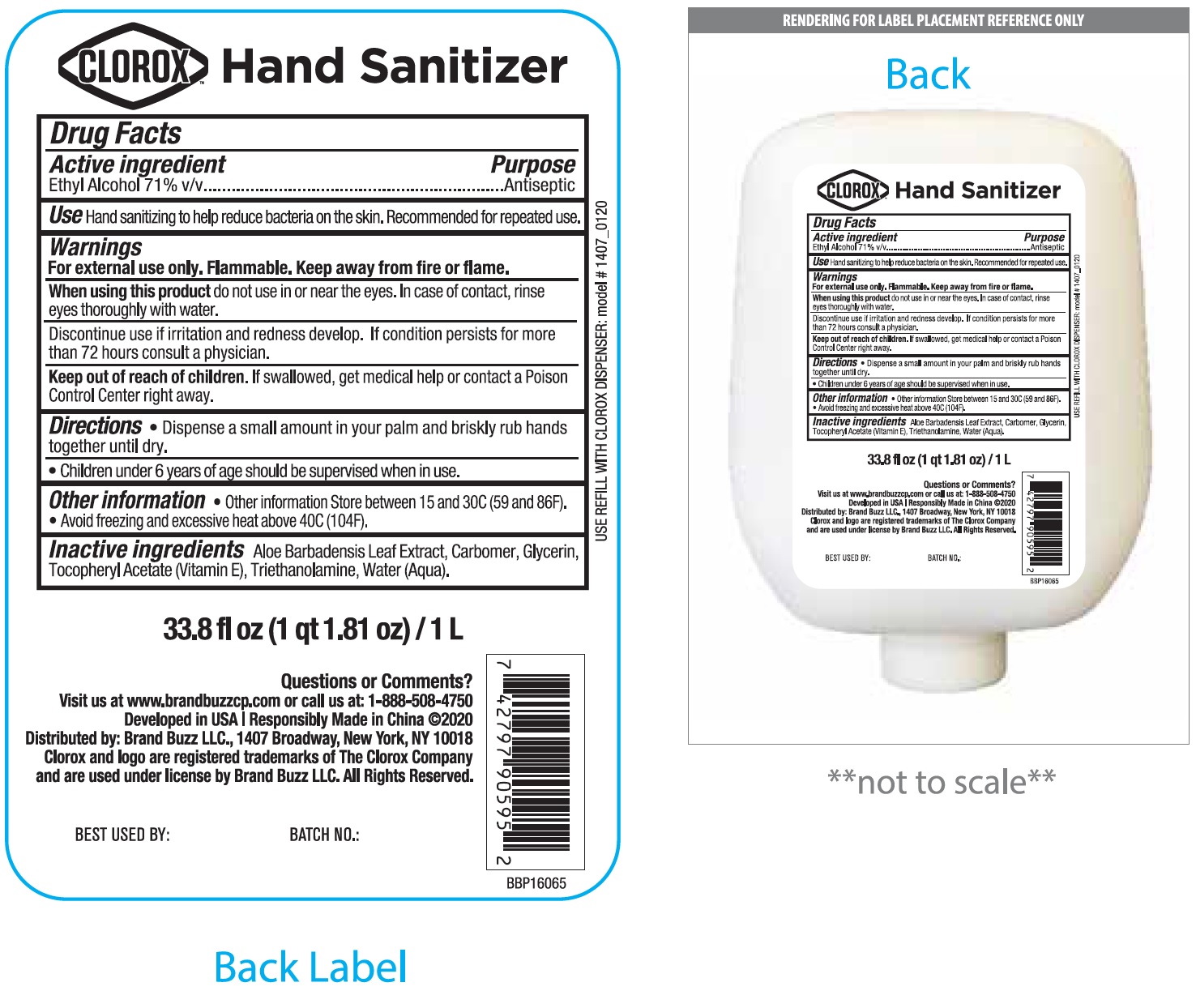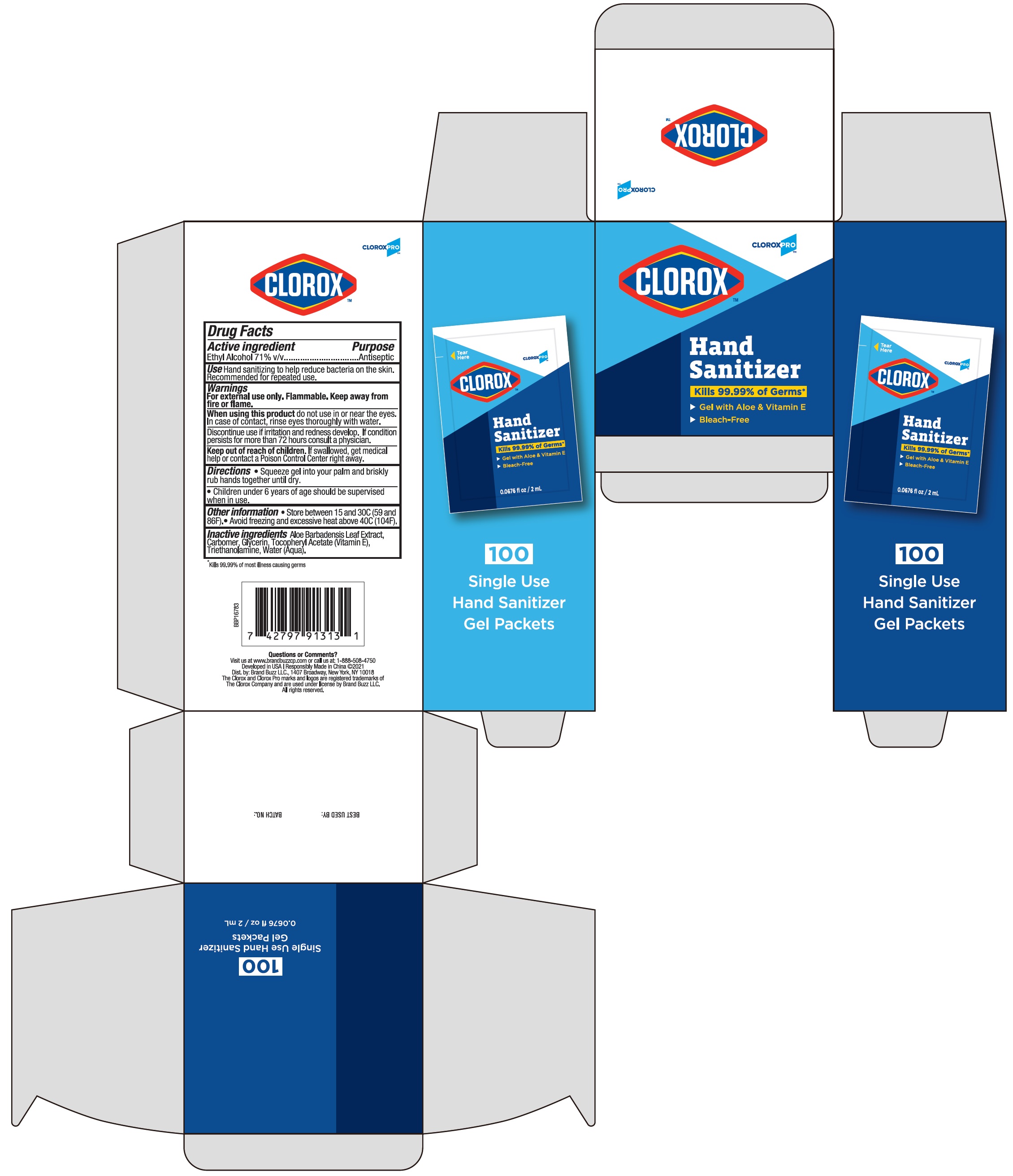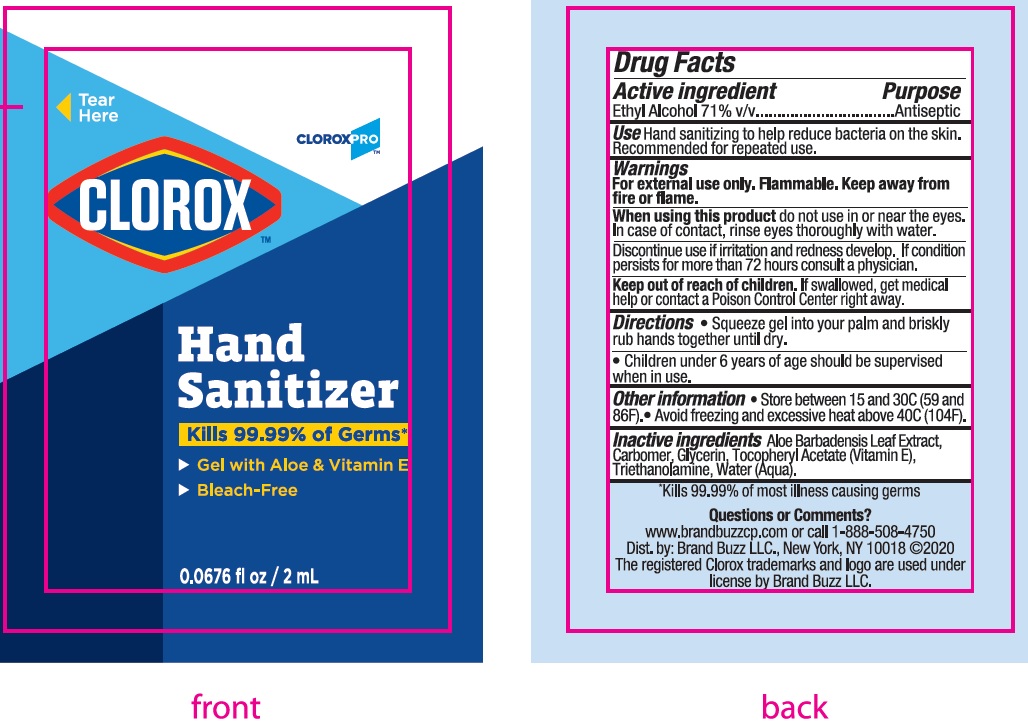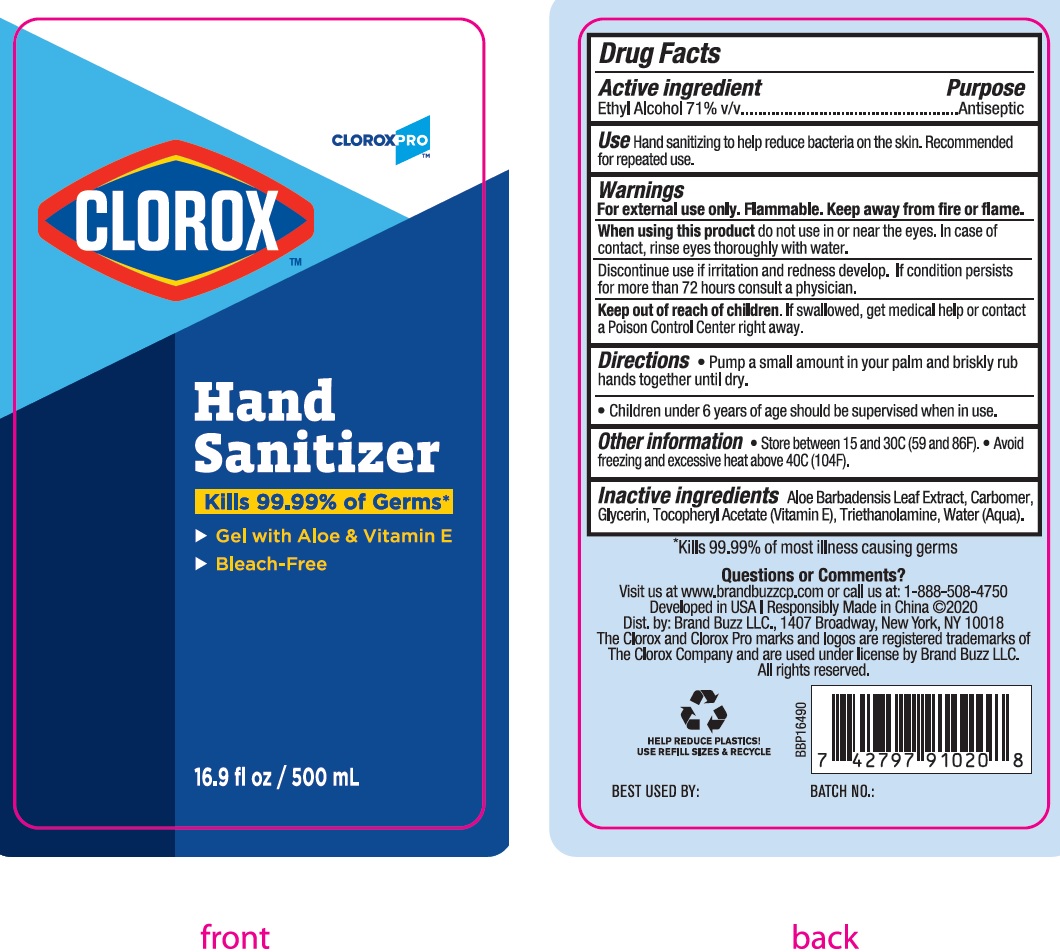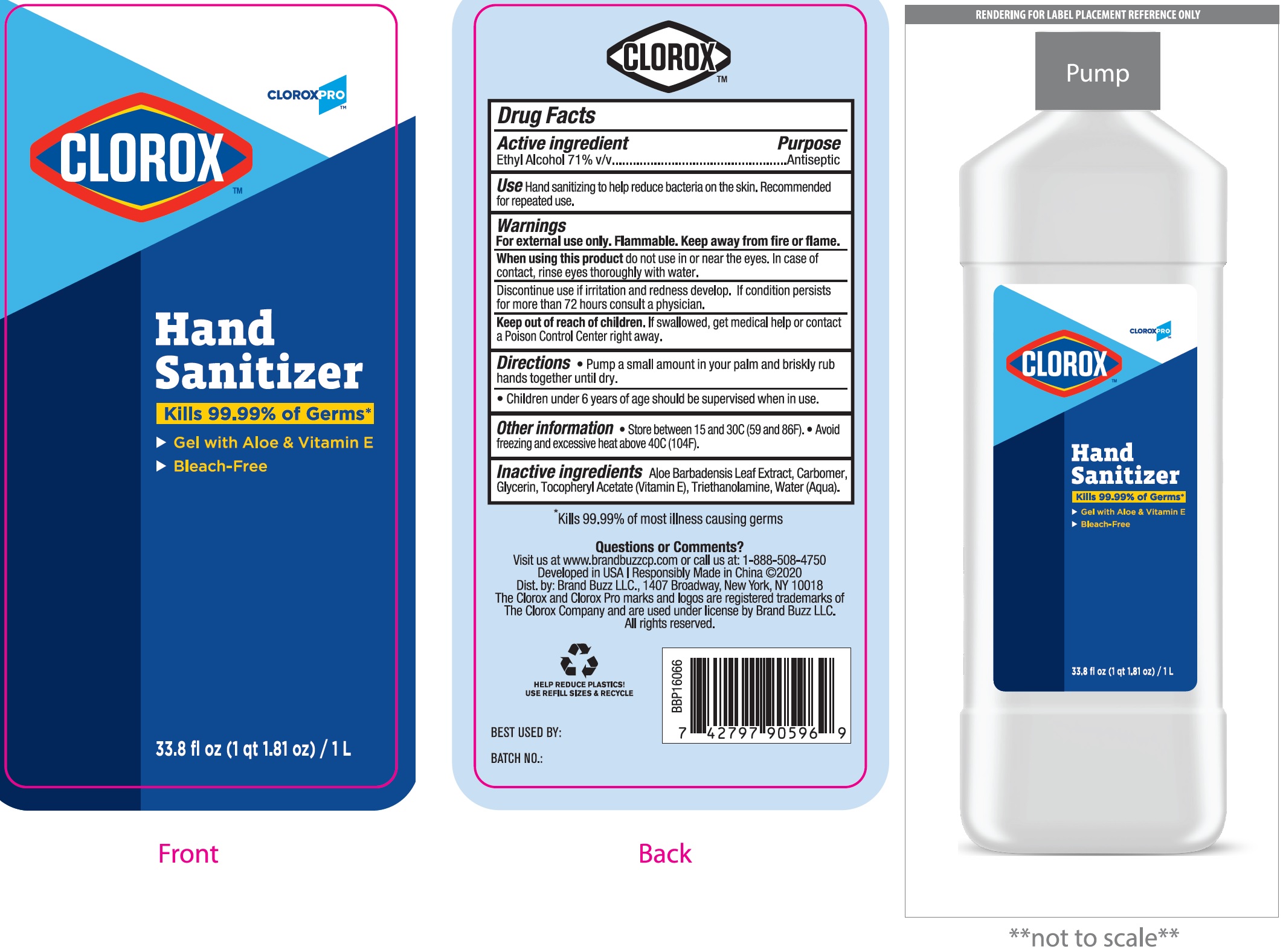 DRUG LABEL: Clorox Hand Sanitizer
NDC: 69540-0025 | Form: GEL
Manufacturer: Brand Buzz LLC
Category: otc | Type: HUMAN OTC DRUG LABEL
Date: 20250303

ACTIVE INGREDIENTS: ALCOHOL 71 mL/100 mL
INACTIVE INGREDIENTS: CARBOMER HOMOPOLYMER, UNSPECIFIED TYPE; ALOE VERA LEAF; GLYCERIN; .ALPHA.-TOCOPHEROL ACETATE; TROLAMINE; WATER

Clorox Hand Sanitizer

Active ingredient

Ethyl Alcohol 71% v/v

Purpose

Antiseptic

Use

Hand sanitizer to help reduce bacteria on the skin. Recommended for repeated use.

Warnings

For external use only. Flammable. Keep away from fire or flame.

When using this product

do not use in or near the eyes. In case of contact, rinse eyes thoroughly with water.

Discontinue use

if irritation and redness develop. If condition persists for more than 72 hours consult a physician.

Keep out of reach of children.

If swallowed, get medical help or contact a Poison Control Center right away

Directions

- Squeeze gel into your palm and briskly rub hands together until dry.
- Children under 6 years of age should be supervised when in use.

Other information

- Store between 15 and 30C (59 and 86F).
- Avoid freezing and excessive heat above 40C (104F).

Inactive ingredients

Aloe Barbadensis Leaf Extract, Carbomer, Glycerin, Tocopheryl Acetate (Vitamin E), Triethanolamine, Water (Aqua).